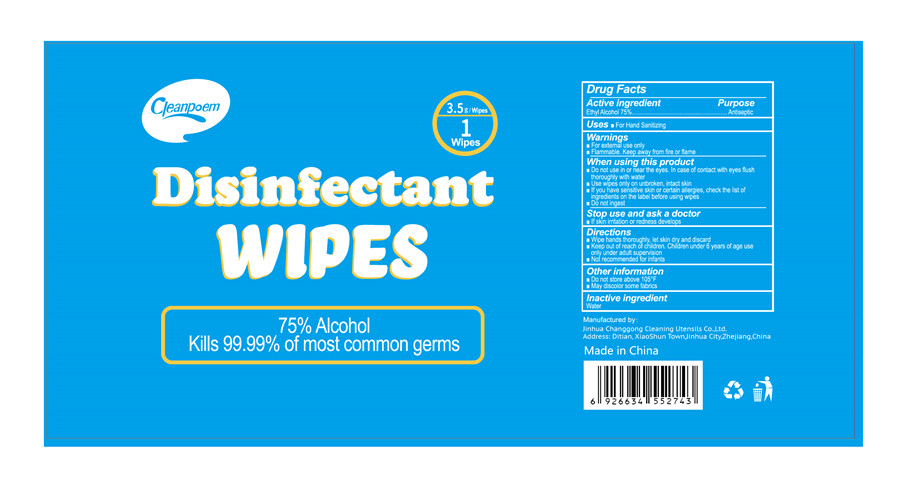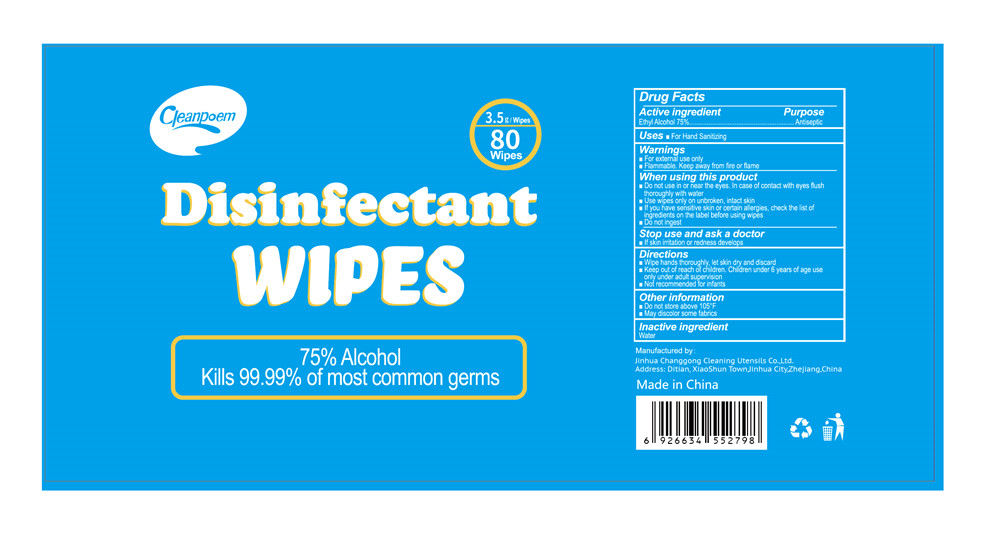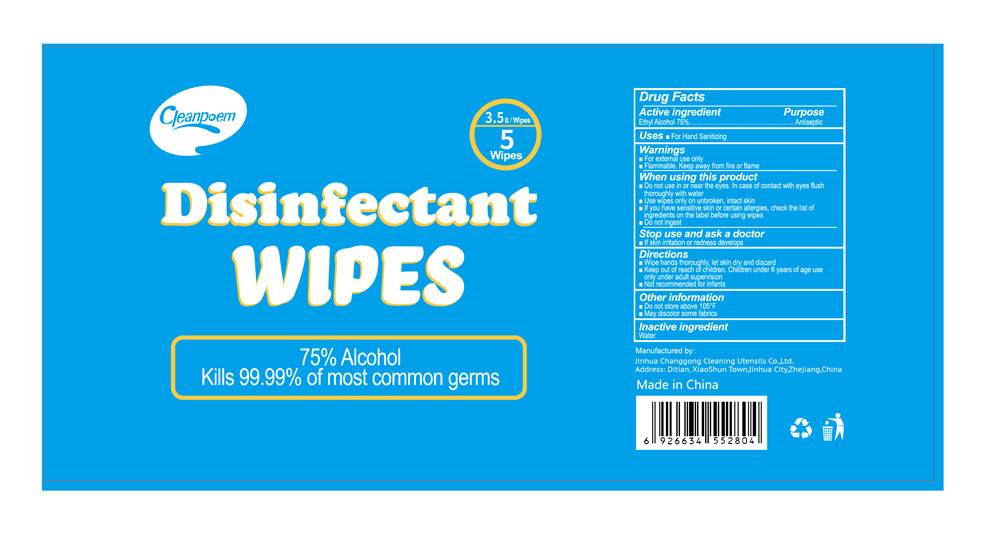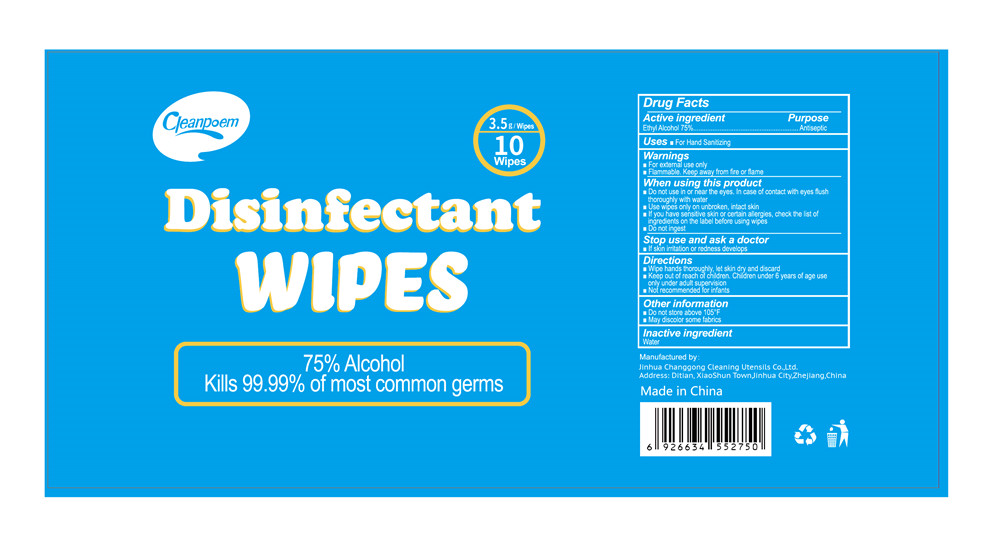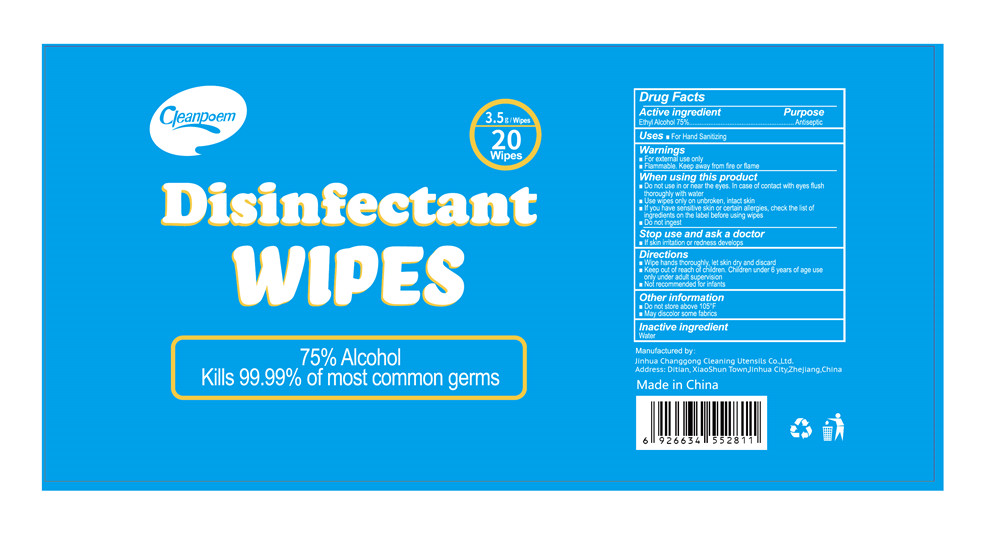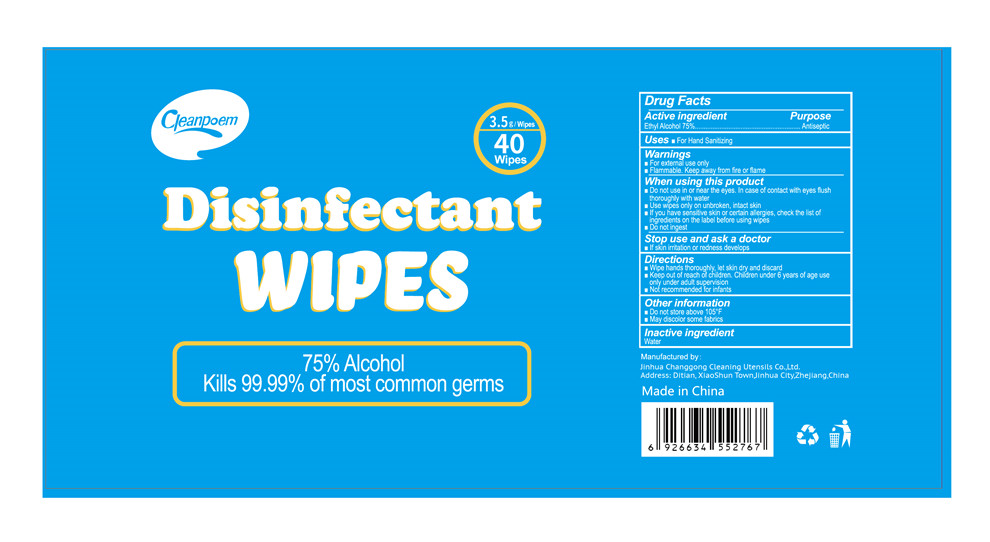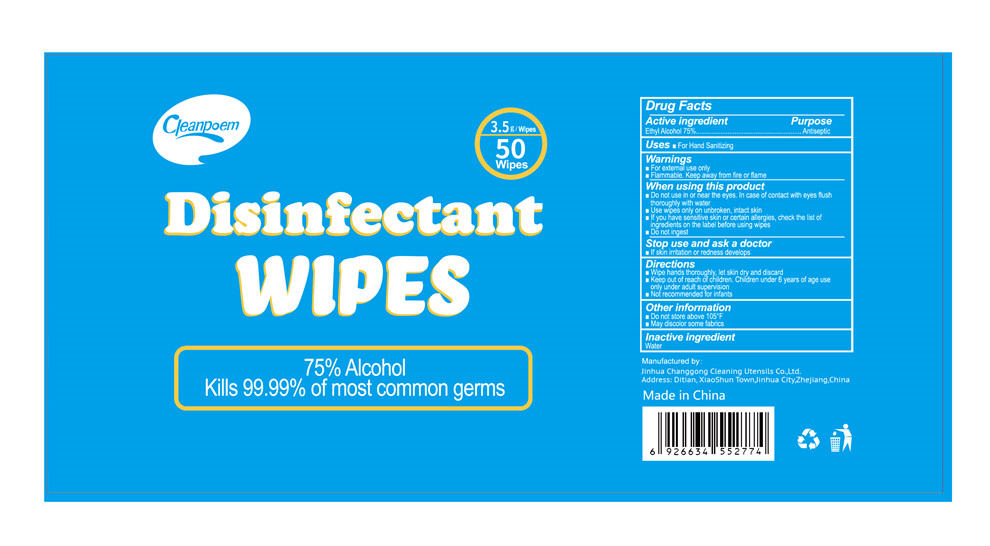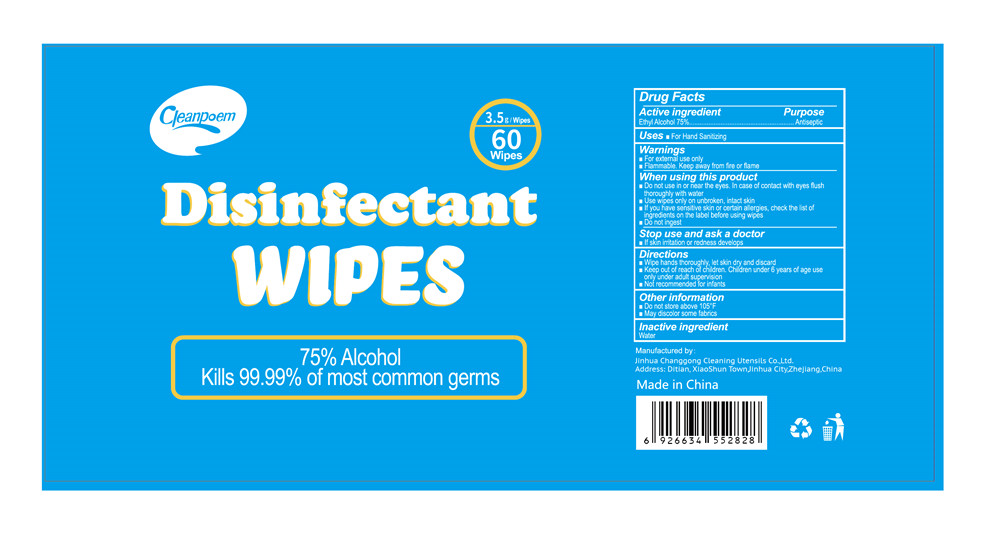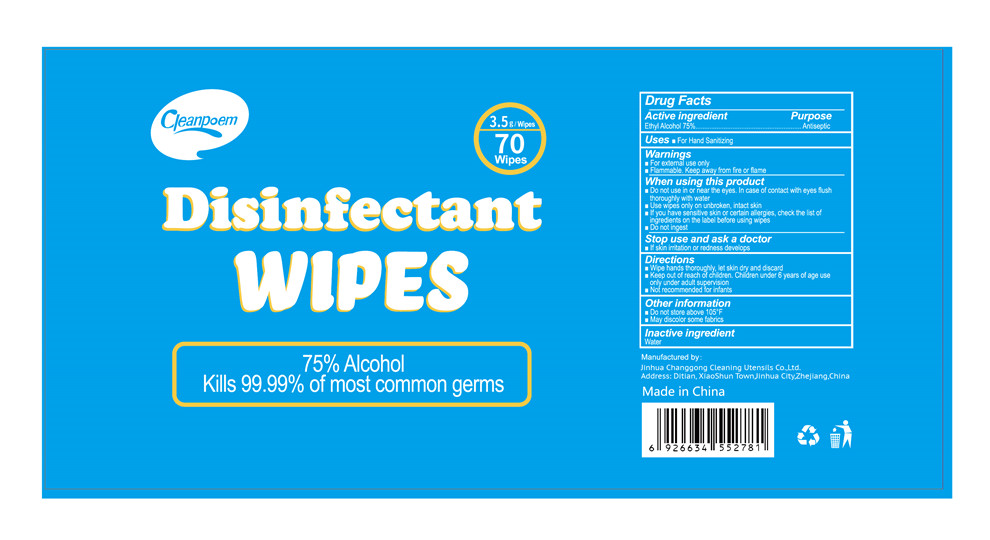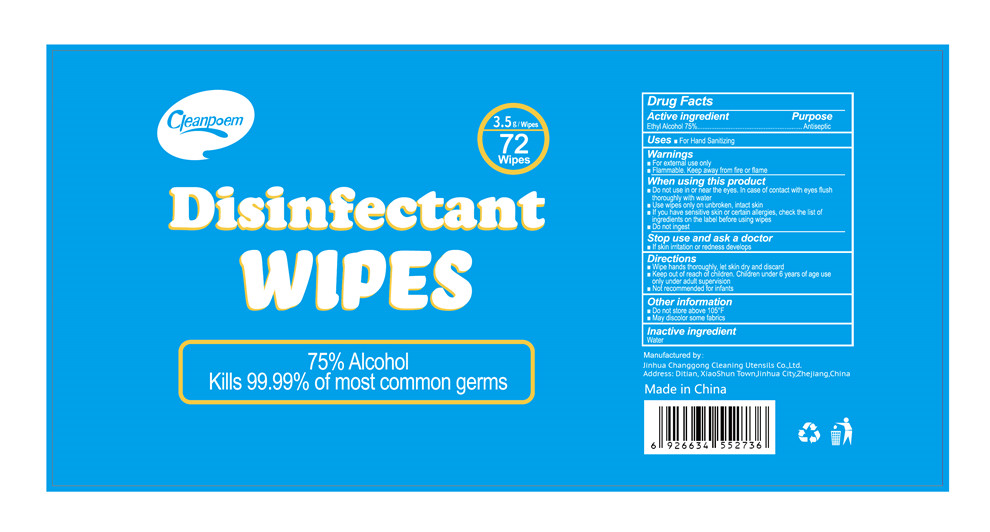 DRUG LABEL: disinfectant wipes
NDC: 78505-001 | Form: CLOTH
Manufacturer: JINHUA CHANG GONG CLEANING UTENSILS CO.,LTD
Category: otc | Type: HUMAN OTC DRUG LABEL
Date: 20200528

ACTIVE INGREDIENTS: ALCOHOL 75 g/100 g
INACTIVE INGREDIENTS: WATER

disinfectant wipes

Active ingredient

Ethyl Alcohol 75%

Purpose

Antiseptic

Uses

For Hand Sanitizing

Warnings

For external use only.

Flammable.Keep away from fire or flame.

When using this product

Do not use in or near the eyes.In case of contact with eyes flush thoroughly with water

Use wipes only on unbroken, intact skin

lf you have sensitive skin or certain allergies,

check the list of ingredients on the label before using wipes

Do not ingest

Stop use and ask a doctor

lf skin irritation or redness develops

Directions

Wipe hands thoroughly, let skin dry and discard

Keep out of reach of children.Children under 6 years of age use

only under adult supervision

Not recommended for infants

Other information

Do not store above 105°F

May discolor some fabrics

Inactive ingredient

Water